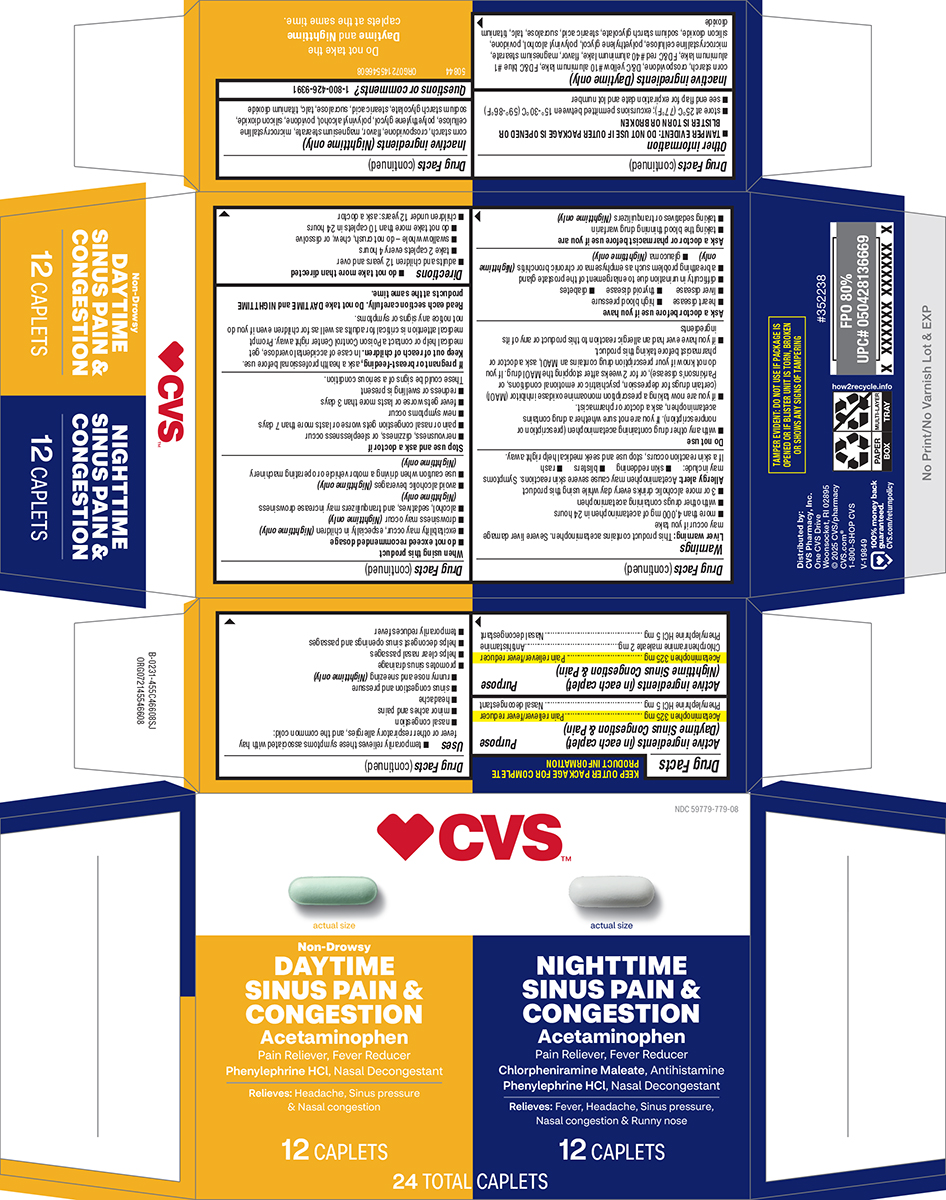 DRUG LABEL: SINUS PAIN AND CONGESTION
NDC: 59779-779 | Form: KIT | Route: ORAL
Manufacturer: CVS Pharmacy
Category: otc | Type: HUMAN OTC DRUG LABEL
Date: 20251202

ACTIVE INGREDIENTS: ACETAMINOPHEN 325 mg/1 1; PHENYLEPHRINE HYDROCHLORIDE 5 mg/1 1; ACETAMINOPHEN 325 mg/1 1; CHLORPHENIRAMINE MALEATE 2 mg/1 1; PHENYLEPHRINE HYDROCHLORIDE 5 mg/1 1
INACTIVE INGREDIENTS: STARCH, CORN; CROSPOVIDONE, UNSPECIFIED; D&C YELLOW NO. 10 ALUMINUM LAKE; FD&C BLUE NO. 1 ALUMINUM LAKE; FD&C RED NO. 40 ALUMINUM LAKE; MAGNESIUM STEARATE; MICROCRYSTALLINE CELLULOSE; POLYETHYLENE GLYCOL, UNSPECIFIED; POLYVINYL ALCOHOL, UNSPECIFIED; POVIDONE, UNSPECIFIED; SILICON DIOXIDE; SODIUM STARCH GLYCOLATE TYPE A POTATO; STEARIC ACID; SUCRALOSE; TALC; TITANIUM DIOXIDE; STARCH, CORN; CROSPOVIDONE, UNSPECIFIED; MAGNESIUM STEARATE; MICROCRYSTALLINE CELLULOSE; POLYETHYLENE GLYCOL, UNSPECIFIED; POLYVINYL ALCOHOL, UNSPECIFIED; POVIDONE, UNSPECIFIED; SILICON DIOXIDE; SODIUM STARCH GLYCOLATE TYPE A POTATO; STEARIC ACID; SUCRALOSE; TALC; TITANIUM DIOXIDE

SINUS PAIN AND CONGESTION

Active ingredients (in each caplet) (Daytime Sinus Congestion & Pain)

Acetaminophen 325 mg
Phenylephrine HCl 5 mg

Purpose

Pain reliever/fever reducer
Nasal decongestant

Active ingredients (in each caplet) (Nighttime Sinus Congestion & Pain)

Acetaminophen 325 mg
Chlorpheniramine maleate 2 mg
Phenylephrine HCl 5 mg

Purpose

Pain reliever/fever reducer
Antihistamine
Nasal decongestant

Uses

- temporarily relieves these symptoms associated with hay fever or other respiratory allergies, and the common cold:
  - nasal congestion
  - headache
  - minor aches and pains
  - sinus congestion and pressure
  - runny nose and sneezing (Nighttime only)
- promotes sinus drainage
- helps clear nasal passages
- helps decongest sinus openings and passages
- temporarily reduces fever

Warnings

Liver warning: This product contains acetaminophen. Severe liver damage may occur if you take

- more than 4,000 mg of acetaminophen in 24 hours
- with other drugs containing acetaminophen
- 3 or more alcoholic drinks every day while using this product

Allergy alert: Acetaminophen may cause severe skin reactions. Symptoms may include:

- skin reddening
- blisters
- rash

If a skin reaction occurs, stop use and seek medical help right away.

Do not use

- if you have ever had an allergic reaction to this product or any of its ingredients
- with any other drug containing acetaminophen (prescription or nonprescription). If you are not sure whether a drug contains acetaminophen, ask a doctor or pharmacist.
- if you are now taking a prescription monoamine oxidase inhibitor (MAOI) (certain drugs for depression, psychiatric or emotional conditions, or Parkinson's disease), or for 2 weeks after stopping the MAOI drug. If you do not know if your prescription drug contains an MAOI, ask a doctor or pharmacist before taking this product.

Ask a doctor before use if you have

- heart disease
- high blood pressure
- liver disease
- thyroid disease
- diabetes
- difficulty in urination due to enlargement of the prostate gland
- a breathing problem such as emphysema or chronic bronchitis (Nighttime only)
- glaucoma (Nighttime only)

Ask a doctor or pharmacist before use if you are

- taking the blood thinning drug warfarin
- taking sedatives or tranquilizers (Nighttime only)

When using this product

- do not exceed recommended dosage
- use caution when driving a motor vehicle or operating machinery (Nighttime only)
- drowsiness may occur (Nighttime only)
- excitability may occur, especially in children (Nighttime only)
- alcohol, sedatives, and tranquilizers may increase drowsiness (Nighttime only)
- avoid alcoholic beverages (Nighttime only)

Stop use and ask a doctor if

- nervousness, dizziness, or sleeplessness occur
- pain or nasal congestion gets worse or lasts more than 7 days
- fever gets worse or lasts more than 3 days
- redness or swelling is present
- new symptoms occur

These could be signs of a serious condition.

If pregnant or breast-feeding,

ask a health professional before use.

Keep out of reach of children.

In case of accidental overdose, get medical help or contact a Poison Control Center right away. Prompt medical attention is critical for adults as well as for children even if you do not notice any signs or symptoms.

Read each section carefully. Do not take DAYTIME and NIGHTTIME products at the same time.

Directions

- do not take more than directed
- adults and children 12 years and over
  - take 2 caplets every 4 hours
  - swallow whole - do not crush, chew, or dissolve
  - do not take more than 10 caplets in 24 hours
- children under 12 years: ask a doctor

Other information

- TAMPER EVIDENT: DO NOT USE IF OUTER PACKAGE IS OPENED OR BLISTER IS TORN OR BROKEN
- store at 25ºC (77ºF); excursions permitted between 15º-30ºC (59º-86ºF)
- see end flap for expiration date and lot number

Inactive ingredients (Daytime only)

corn starch, crospovidone, D&C yellow #10 aluminum lake, FD&C blue #1 aluminum lake, FD&C red #40 aluminum lake, flavor, magnesium stearate, microcrystalline cellulose, polyethylene glycol, polyvinyl alcohol, povidone, silicon dioxide, sodium starch glycolate, stearic acid, sucralose, talc, titanium dioxide

Inactive ingredients (Nighttime only)

corn starch, crospovidone, flavor, magnesium stearate, microcrystalline cellulose, polyethylene glycol, polyvinyl alcohol, povidone, silicon dioxide, sodium starch glycolate, stearic acid, sucralose, talc, titanium dioxide

Questions or comments?

1-800-426-9391

Principal Display Panel

♥︎CVS™

NDC 59779-779-08

actual size

Non-Drowsy
DAYTIME
SINUS PAIN &
CONGESTION

ACETAMINOPHEN
Pain Reliever, Fever Reducer
Phenylephrine HCl, Nasal Decongestant

Relieves: Headache, Sinus pressure
& Nasal congestion

12 CAPLETS

actual size

NIGHTTIME
SINUS PAIN &
CONGESTION

ACETAMINOPHEN
Pain Reliever, Fever Reducer
Chlorpheniramine Maleate, Antihistamine
Phenylephrine HCl, Nasal Decongestant

Relieves: Fever, Headache, Sinus pressure,
Nasal congestion & Runny nose

12 CAPLETS

24 TOTAL CAPLETS

TAMPER EVIDENT: DO NOT USE IF PACKAGE IS
OPENED OR IF BLISTER UNIT IS TORN, BROKEN
OR SHOWS ANY SIGNS OF TAMPERING

Distributed by:
CVS Pharmacy, Inc.
One CVS Drive
Woonsocket, RI 02895
© 2025 CVS/pharmacy
CVS.com®
1-800-SHOP CVS
V-19849

100% money back
guaranteed.
CVS.com/returnpolicy

50844 ORG072145546608

Do not take the
Daytime and Nighttime
caplets at the same time.

CVS 44-455C466